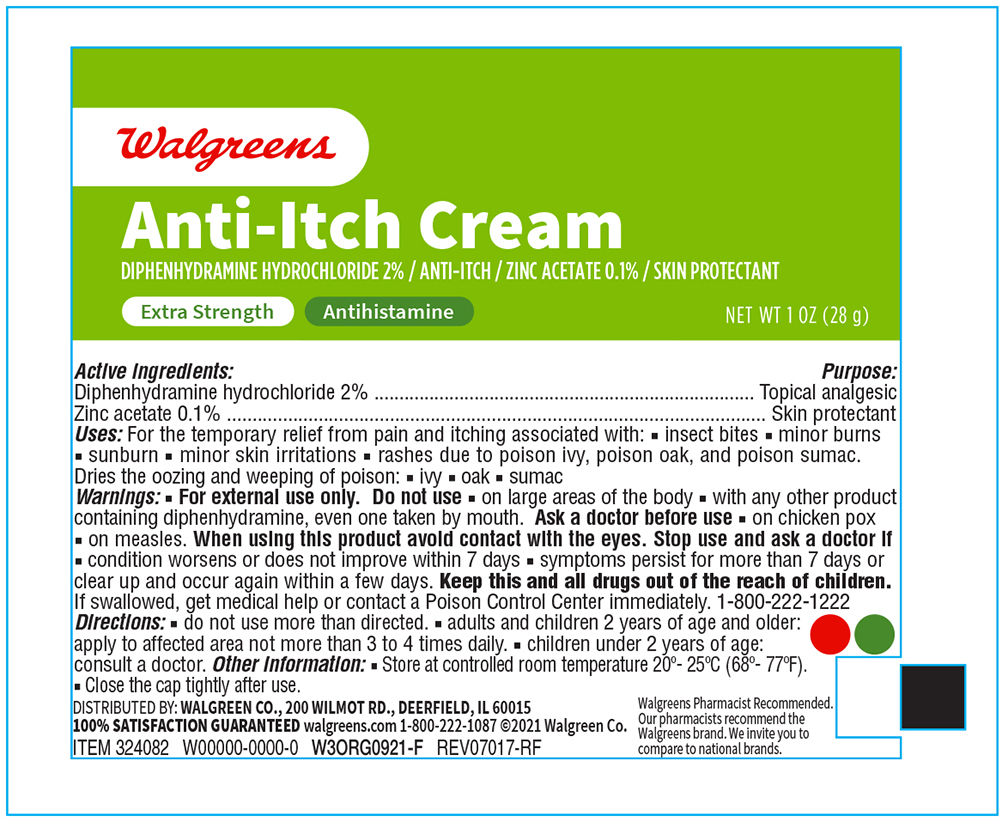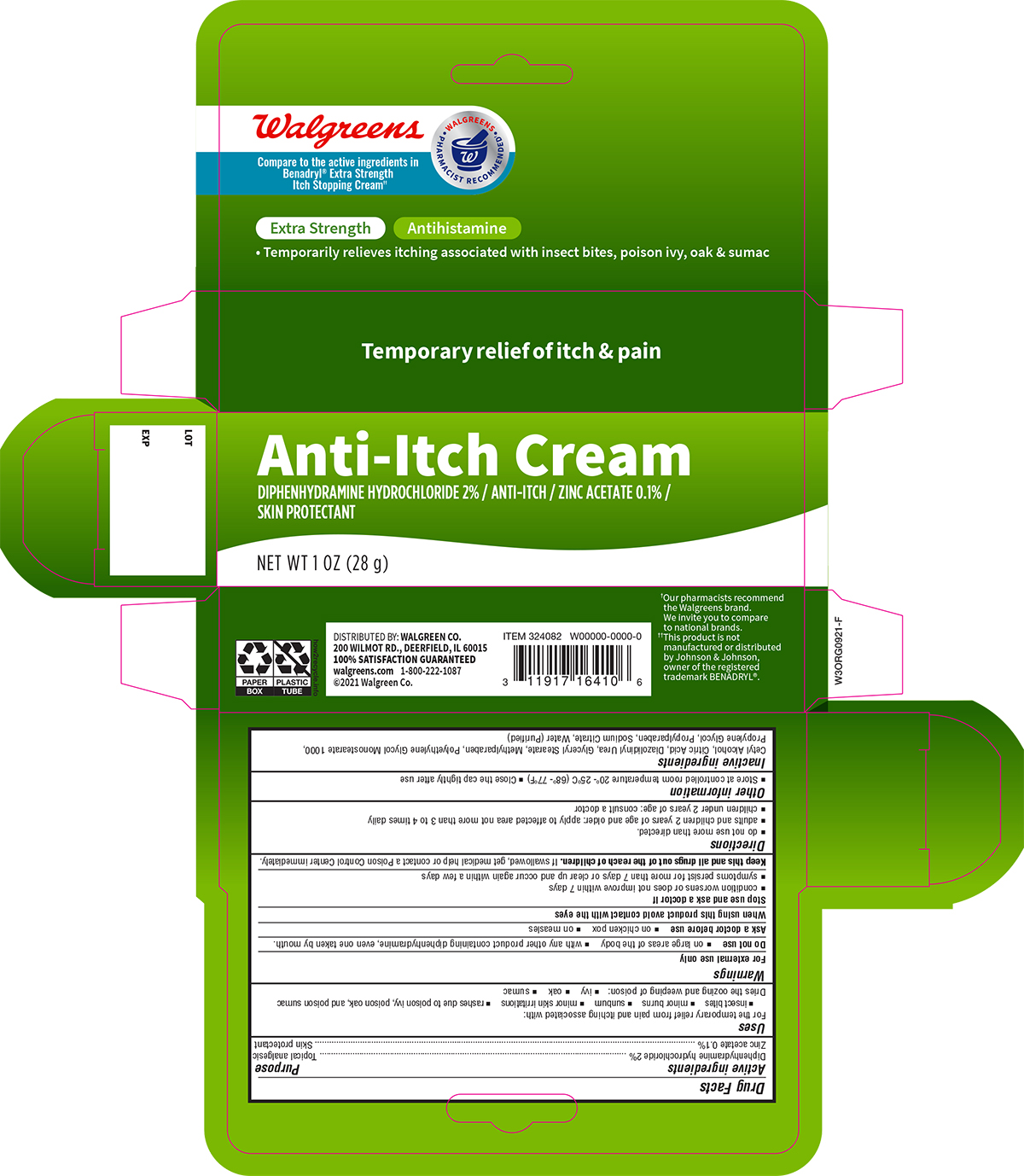 DRUG LABEL: Walgreens Anti Itch Cream
NDC: 0363-2315 | Form: CREAM
Manufacturer: Walgreens Company
Category: otc | Type: HUMAN OTC DRUG LABEL
Date: 20260121

ACTIVE INGREDIENTS: DIPHENHYDRAMINE HYDROCHLORIDE 20 mg/1 g; ZINC ACETATE 1 mg/1 g
INACTIVE INGREDIENTS: CETYL ALCOHOL; DIAZOLIDINYL UREA; CITRIC ACID MONOHYDRATE; METHYLPARABEN; PEG-20 STEARATE; PROPYLENE GLYCOL MONOSTEARATE; PROPYLENE GLYCOL; PROPYLPARABEN; SODIUM CITRATE; WATER

Walgreens Anti Itch Cream

Active ingredients

Diphenhydramine hydrochloride 2%

Zinc Acetate 0.1%

Purpose

Topical analgesic

Skin protectant

Uses

For temporary relief from pain and itching associated with :

- insect bites
- minor burns
- sunburn
- minor skin irritations
- rashes due to poison ivy, poison oak, and poison sumac

Dries the oozing and weeping of poison

- ivy
- oak
- sumac

Warnings

For external use only

Do not use

- on large areas of the body
- with any other product containing diphenhydramine , even one taken by the mouth.

Ask a Doctor before use

- on chicken pox
- on measles

When using this product avoid contact with eyes.

Stop use and ask a doctor if

- conditions worsen or does not improve within 7 days
- symptoms persist for more than 7 days or clear up and occur agian within a few days

Keep this and all drugs out of the reach of children.

If swallowed get medical help or contact a Poison Control Center immediately.

Directions

- do not use more than directed
- adults and children 2 years of age and older; apply to affected areas not more than 3 to 4 times daily
- children under 2 years of age , consult a doctor

Other Information

- Store at controlled room temperature 20°-25°C (68° - 77°F)
- Close the cap tightly after use

Inactive ingredients

Cetyl Alcohol, Citric Acid, Diazolldinyl Urea, Glyceral Stearate, Methylparaben, Polyethylene Glycol Monsterate 1000, Sodium Citrate, Water

(Purified)

Other Information

- Store at controlled room temperature 20° -25°C (68°-77°F)
- Close Cap tightly after use

Principal Display Panel

Walgreens NDC 0363-2315-28

Anti Itch Cream

Diphenhydramine HCL 2.0% Topical Analgesic

Zinc Acetate 0.1% Skin Protectant

NET WT 1.0 oz (28g)